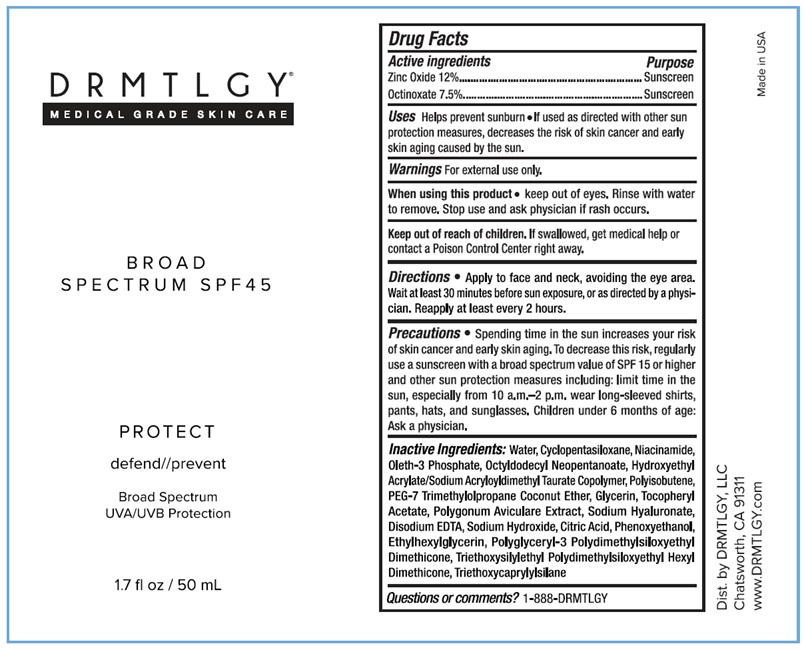 DRUG LABEL: Broad Spectrum SPF45
NDC: 83286-008 | Form: GEL
Manufacturer: Drmtlgy, LLC
Category: otc | Type: HUMAN OTC DRUG LABEL
Date: 20250501

ACTIVE INGREDIENTS: ZINC OXIDE 12 g/100 g; OCTINOXATE 7.5 g/100 g
INACTIVE INGREDIENTS: WATER; CYCLOMETHICONE 5; NIACINAMIDE; OLETH-3 PHOSPHATE; OCTYLDODECYL NEOPENTANOATE; HYDROXYETHYL ACRYLATE/SODIUM ACRYLOYLDIMETHYL TAURATE COPOLYMER (100000 MPA.S AT 1.5%); POLYISOBUTYLENE (1000 MW); PEG-7 TRIMETHYLOLPROPANE COCONUT ETHER; GLYCERIN; .ALPHA.-TOCOPHEROL ACETATE; POLYGONUM AVICULARE TOP; HYALURONATE SODIUM; EDETATE DISODIUM; SODIUM HYDROXIDE; CITRIC ACID MONOHYDRATE; PHENOXYETHANOL; ETHYLHEXYLGLYCERIN; POLYGLYCERYL-3 POLYDIMETHYLSILOXYETHYL DIMETHICONE (4000 MPA.S); TRIETHOXYSILYLETHYL POLYDIMETHYLSILOXYETHYL HEXYL DIMETHICONE; TRIETHOXYCAPRYLYLSILANE

DRMTLGY® Broad Spectrum SPF45

Active ingredients

Zinc Oxide 12%

Octinoxate 7.5%

Purpose

Sunscreen

Uses

Helps prevent sunburn. • If used as directed with other sun protection measures, decreases the risk of skin cancer and early skin aging caused by the sun.

Warnings

For external use only.

When using this product • keep out of eyes. Rinse with water to remove. Stop use and ask physician if rash occurs.

Keep out of reach of children. If swallowed, get medical help or contact a Poison Control Center right away.

Directions

• Apply to face and neck, avoiding the eye area. Wait at least 30 minutes before sun exposure, or as directed by a physician. Reapply at least every 2 hours.

Precautions

• Spending time in the sun increases your risk of skin cancer and early skin aging. To decrease this risk, regularly use a sunscreen with a broad spectrum value of SPF 15 or higher and other sun protection measures including: limit time in the sun, especially from 10 a.m.-2 p.m. wear long-sleeved shirts, pants, hats, and sunglasses. Children under 6 months of age: Ask a physician.

Inactive Ingredients:

Water, Cyclopentasiloxane, Niacinamide, Oleth-3 Phosphate, Octyldodecyl Neopentanoate, Hydroxyethyl Acrylate/Sodium Acryloyldimethyl Taurate Copolymer, Polyisobutene, PEG-7 Trimethylolpropane Coconut Ether, Glycerin, Tocopheryl Acetate, Polygonum Aviculare Extract, Sodium Hyaluronate, Disodium EDTA, Sodium Hydroxide, Citric Acid, Phenoxyethanol, Ethylhexylglycerin, Polyglyceryl-3 Polydimethylsiloxyethyl Dimethicone, Triethoxysilylethyl Polydimethylsiloxyethyl Hexyl Dimethicone, Triethoxycaprylylsilane

Questions or comments?

1-888-DRMTLGY

MEDICAL GRADE SKIN CARE

PROTECT

defend//prevent

Broad Spectrum
UVA/UVB Protection

Dist. by DRMTLGY, LLC
Chatsworth, CA 91311
www.DRMTLGY.com

Made in USA